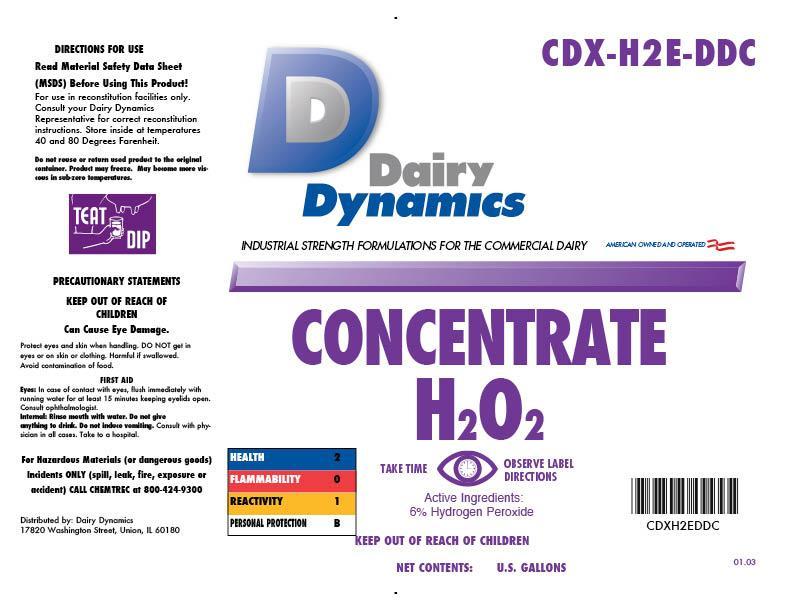 DRUG LABEL: Concentrate H2O2
NDC: 67351-288 | Form: CONCENTRATE
Manufacturer: Dairy Dynamics L.L.C.
Category: animal | Type: OTC ANIMAL DRUG LABEL
Date: 20150120

ACTIVE INGREDIENTS: HYDROGEN PEROXIDE 14.0 g/1 L
INACTIVE INGREDIENTS: WATER; EDETATE SODIUM; UREA; GLYCERIN; SODIUM LAURETH-3 SULFATE; LACTIC ACID; SODIUM HYDROXIDE; FD&C YELLOW NO. 6

Dairy Dynamics
Concentrate H202

WARNINGS AND PRECAUTIONS

Dairy Dynamics

INDUSTRIAL STRENGTH FORMULATIONS FOR THE COMMERCIAL DAIRY

AMERICAN OWNED AND OPERATED

DIRECTIONS FOR USE

Read Material Safety Data Sheet (MSDS) Before Using This Product!

For use in reconstitution facilities only. Consult your Dairy Dynamics Representative for correct reconstitution instructions. Store inside of temperatures 40 and 80 degrees Farenheit.

Do not reuse or return used product to the original container. Product may freeze. May become more viscous in sub-zero temperatures.

TEAT DIP

PRECAUTIONS

PRECAUTINARY STATEMENTS

KEEP OUT OF REACH OF CHILDREN

Can Cause Eye Damage.

Protect eyes and skin when handling. DO NOT get in eyes or on skin or clothing. Harmful if swallowed. Avoid contamination of food.

FIRST AID

Eyes: in case of contact with eyes, flush immediately with running water for about 15 minutes keeping eyelids open. Consult ophthalmologist.

Internal: Rinse mouth with water. Do not give anything to drink. Do not induce vomiting. Consult with physician in all cases. Take to a hospital.

For Hazardous Materials (or dangerous goods) Incidents ONLY (spill, leak, fire, exposure or accident) CALL CHEMTREC at 800-424-9300

HEALTH 2

FLAMMABILITY 0

REACTIVITY 1

PERSONAL PROTECTION B

Distributed by: Dairy Dynamics

17820 Washington Street, Union, IL 60180

TAKE TIME OBSERVE LABEL DIRECTIONS

Active Ingredients: 5% Hydrogen Peroxide

KEEP OUT OF REACH OF CHILDREN

NET CONTENTS: U.S. GALLONS

CDX-H2E-DDC

CDXH2DDC

01.03